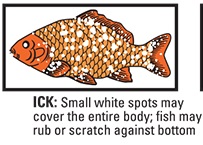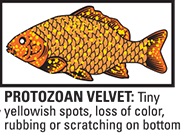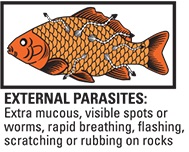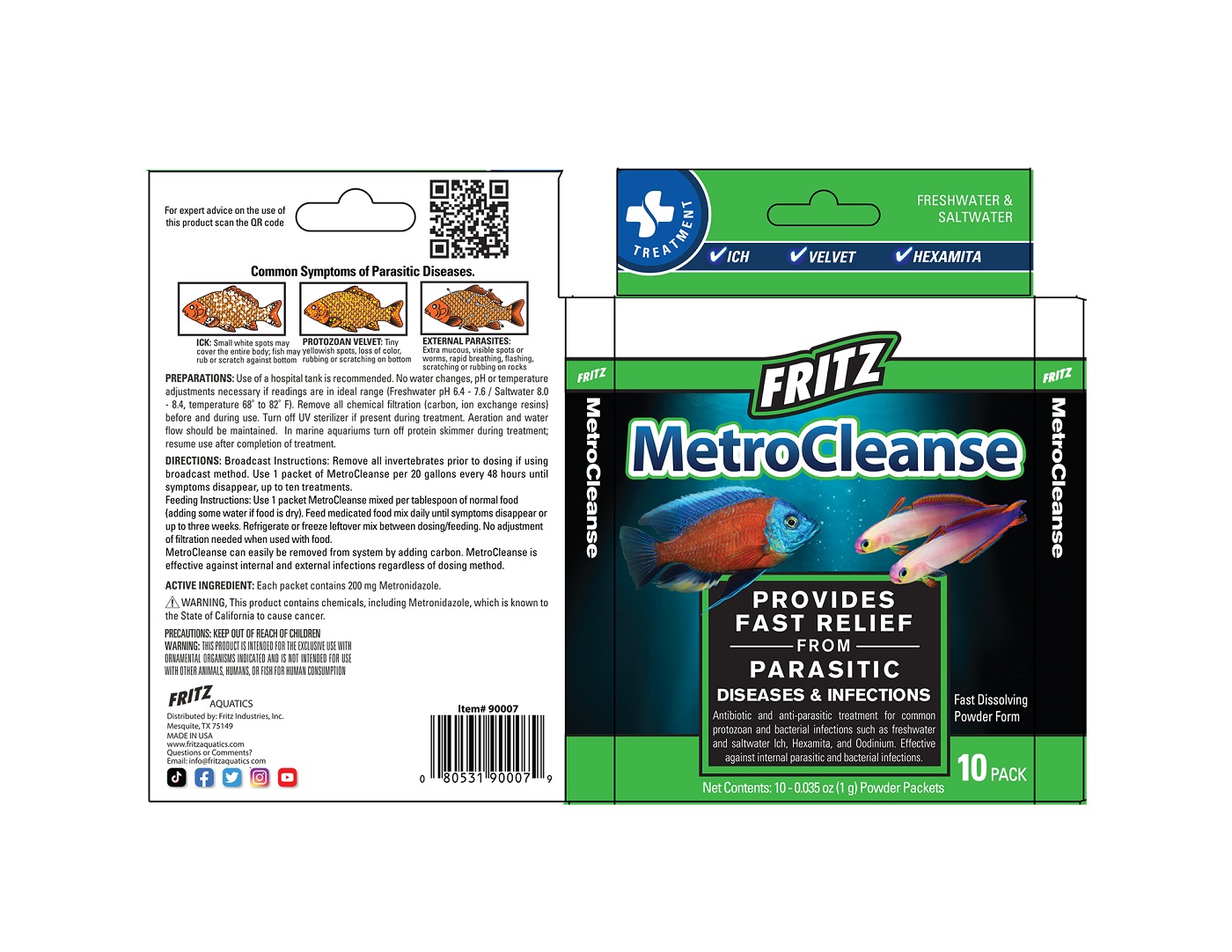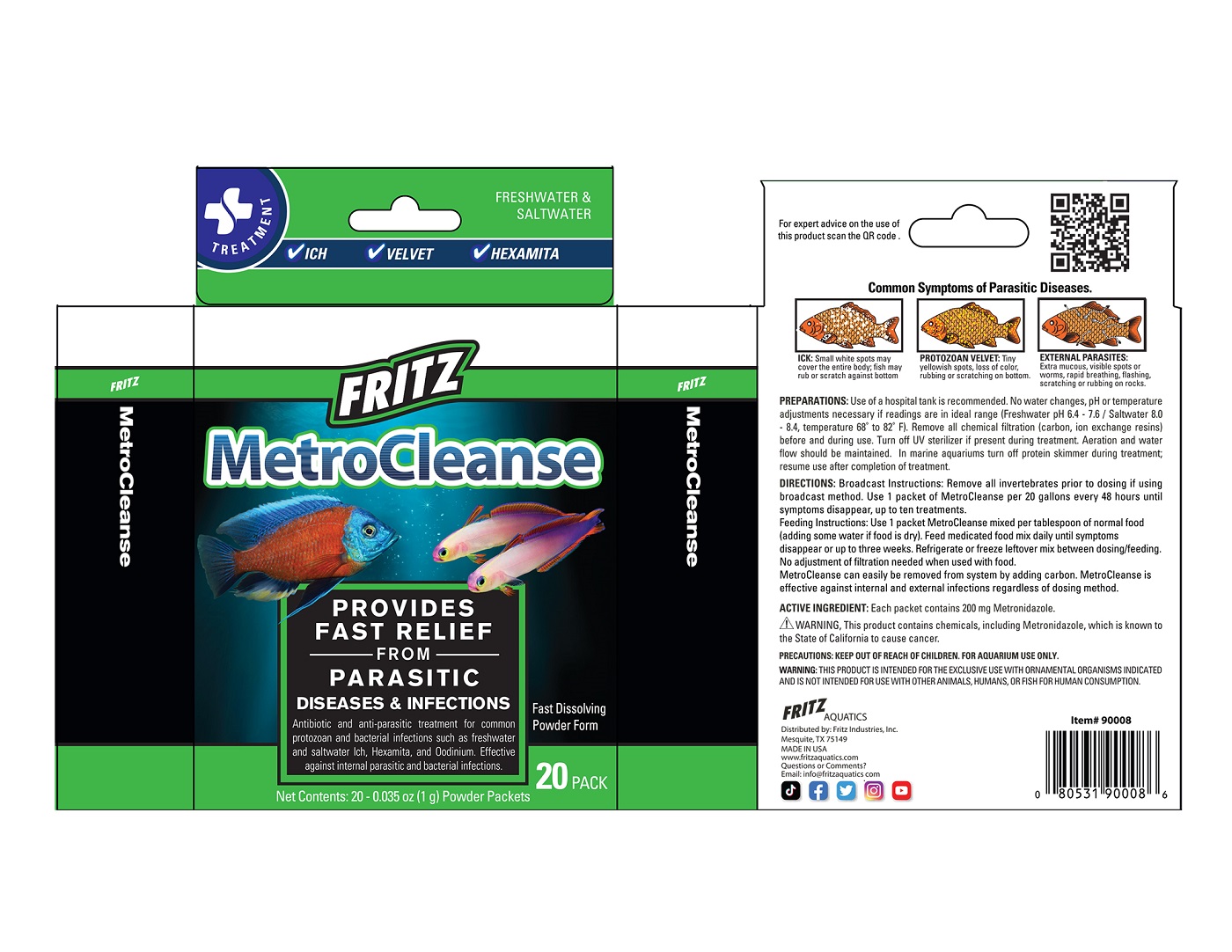 DRUG LABEL: MetroCleanse
NDC: 53745-016 | Form: POWDER
Manufacturer: Fritz Industries
Category: animal | Type: OTC ANIMAL DRUG LABEL
Date: 20211206

ACTIVE INGREDIENTS: METRONIDAZOLE 200 mg/1 g
INACTIVE INGREDIENTS: SILICON DIOXIDE; DEXTROSE; MALTODEXTRIN

MetroCleanse

Indications:

Common Symptoms of Parasitic Diseases.

ICK: Small white spots may cover the entire body; fish may rub or scratch against bottom
PROTOZOAN VLVET: Tiny yellowish spots loss of color, rubbing or scratching on bottom
EXTERNAL PARASITES: Extra mucous, visible spots or worms, rapid breathing, flashing, scratching or rubbing on rocks

PREPARATIONS:

Use of a hospital tank is recommended. No water changes, pH or temperature adjustments necessary if readings are in ideal range (Freshwater pH 6.4 - 7.6 / Saltwater 8.0 - 8.4, temperature 68° to 82° F). Remove all chemical filtration (carbon, ion exchange resins) before and during use.
Turn off UV sterilizer if present during treatment. Aeration and water flow should be maintained.

In marine aquariums turn off protein skimmer during treatment; resume use after completion of treatment.

DIRECTIONS:

Broadcast Instructions: Remove all invertebrates prior to dosing if using broadcast method. Use 1 packet of MetroCleanse mixed per tablespoon of normal food (adding some water if food is dry). Feed medicated food mix daily until symptoms disappear or up to three weeks. Refrigerate or
freeze leftover mix between dosing/feeding. No adjustment of filtration needed when used with food.

MetroCleanse can easily be removed from system by adding carbon. MetroCleanse is effective against internal and external infections regardless of dosing method.

ACTIVE INGREDIENT:

Each packet contains 200 mg Metronidazole.

WARNING

This product contains chemicals, including Metronidazole, which is known to the State of California to cause cancer.

PRECAUTIONS:

KEEP OUT OF REACH OF CHILDREN

WARNING:

THIS PRODUCT IS INTENDED FOR THE EXCLUSIVE USE WITH ORNAMENTAL ORGANISMS INDICATED AND IS NOT INTENDED FOR USE WITH OTHER ANIMALS, HUMANS, OR FISH FOR HUMAN CONSUMPTION

FRITZ

MetroCleanse

Provides Fast Relief from Parasitic Diseases & Infections

Antibiotic and anti-parasitic treatment for common protozoan and bacterial infections such as freshwater and saltwater Ich, Hexamita, and Oodinium. Effective agaisnt internal parasitic and bacterial infections.

Net Contents: 10-0.035 oz (1g) Powder Packets

FRITZ AQUATICS
Distributed by: Fritz Industries, Inc.
Mesquite, TX 75149
MADE IN USA
www.fritzaquatics.com
Questions or Comments?
Email: info@fritzaquatics.com